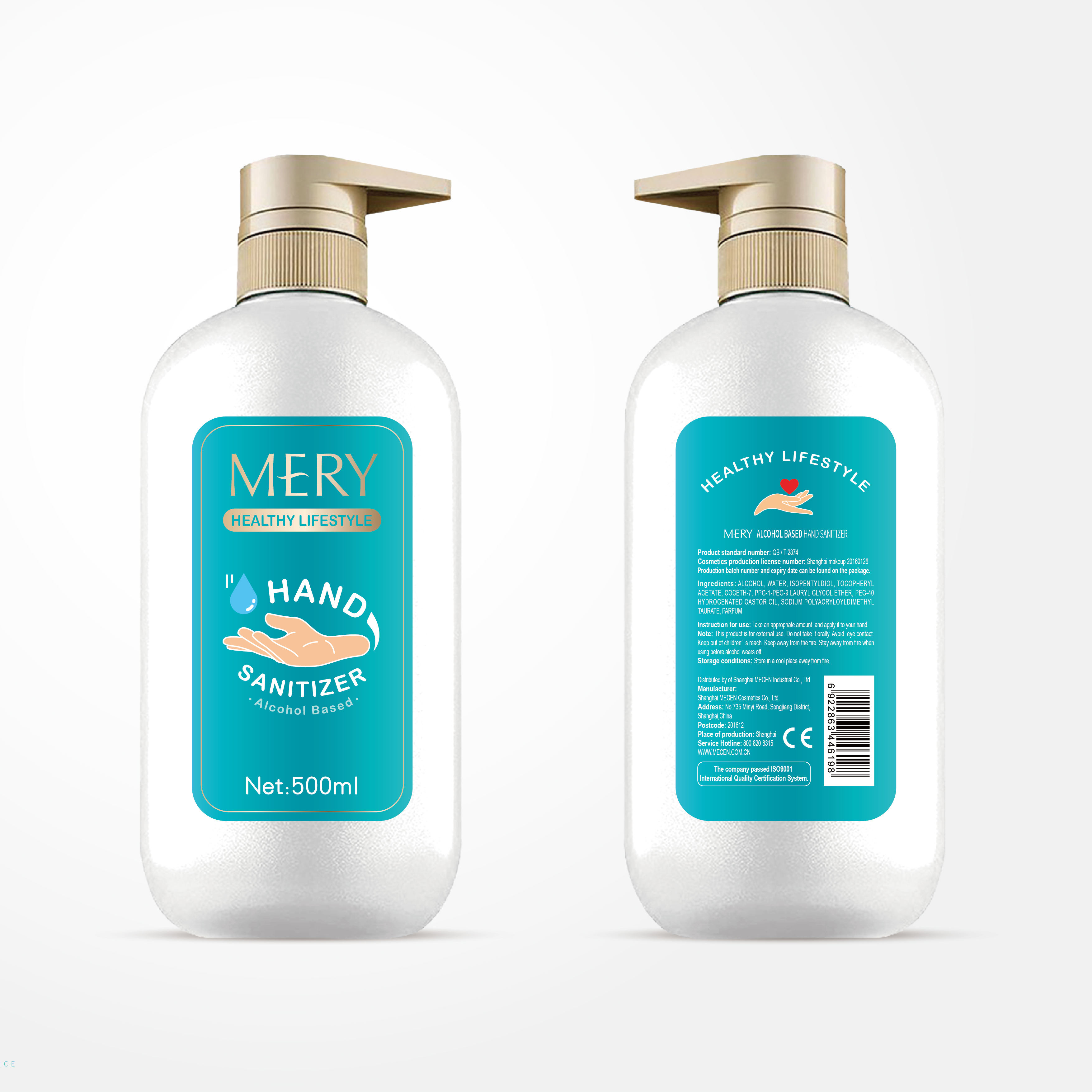 DRUG LABEL: mery alcohol based hand sanitizer
NDC: 54765-011 | Form: LIQUID
Manufacturer: Shanghai Mecen Cosmetics Co., Ltd.
Category: otc | Type: HUMAN OTC DRUG LABEL
Date: 20200416

ACTIVE INGREDIENTS: ALCOHOL 310 mL/500 mL
INACTIVE INGREDIENTS: WATER; .ALPHA.-TOCOPHEROL ACETATE; PPG-1-PEG-9 LAURYL GLYCOL ETHER; CARBOMER HOMOPOLYMER, UNSPECIFIED TYPE; TROLAMINE; ISOPENTYLDIOL; COCETH-7; POLYOXYL 40 HYDROGENATED CASTOR OIL

WARNINGS

This product is for extemal use. Do not take it orally Avoid eye contact.

Keep out of children' s reach. Keep away from the fire.

Stay away from fire when using before alcohol wears off.

INACTIVE INGREDIENT

Water, isoamyl glycol, Tocopherol acetate, coconut alcohol
polyether-7, carbomer, PPG-1-PEG-9 lauryl glycol ether, triethanolamine,
PEC-40 hydrogenated castor oil.

DOSAGE AND ADMINISTRATION

Store in a cool place away from fire.

ACTIVE INGREDIENT

ethanol

keep out of reach of children

INDICATIONS AND USAGE

Take an appropriate amount and apply it to your hand.

PURPOSE

Disinfection
Sterilization
No Rinseing